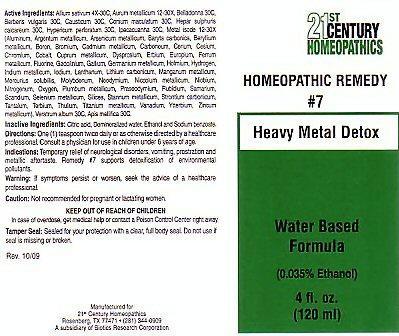 DRUG LABEL: CENTURY 21 HEAVY METAL DETOX
NDC: 63972-007 | Form: LIQUID
Manufacturer: 21st Century Homeopathics, Inc
Category: homeopathic | Type: HUMAN OTC DRUG LABEL
Date: 20100101

ACTIVE INGREDIENTS: GARLIC 30 [hp_C]/5 mL; GOLD 30 [hp_X]/5 mL; ATROPA BELLADONNA 30 [hp_C]/5 mL; BERBERIS VULGARIS ROOT BARK 30 [hp_C]/5 mL; CAUSTICUM 30 [hp_C]/5 mL; CONIUM MACULATUM FLOWERING TOP 30 [hp_C]/5 mL; CALCIUM SULFIDE 30 [hp_C]/5 mL; HYPERICUM PERFORATUM 30 [hp_C]/5 mL; IPECAC 30 [hp_C]/5 mL; ALUMINUM 30 [hp_X]/5 mL; SILVER 30 [hp_X]/5 mL; ARSENIC 30 [hp_X]/5 mL; BARIUM CARBONATE 30 [hp_X]/5 mL; BERYLLIUM 30 [hp_X]/5 mL; BORON 30 [hp_X]/5 mL; BROMINE 30 [hp_X]/5 mL; CADMIUM 30 [hp_X]/5 mL; D&C BLACK NO. 2 30 [hp_X]/5 mL; CERIUM 30 [hp_X]/5 mL; CESIUM 30 [hp_X]/5 mL; CHROMIUM 30 [hp_X]/5 mL; COBALT 30 [hp_X]/5 mL; COPPER 30 [hp_X]/5 mL; DYSPROSIUM 30 [hp_X]/5 mL; ERBIUM 30 [hp_X]/5 mL; EUROPIUM 30 [hp_X]/5 mL; IRON 30 [hp_X]/5 mL; FLUORINE 30 [hp_X]/5 mL; GADOLINIUM 30 [hp_X]/5 mL; GALLIUM 30 [hp_X]/5 mL; GERMANIUM 30 [hp_X]/5 mL; HOLMIUM 30 [hp_X]/5 mL; HYDROGEN 30 [hp_X]/5 mL; INDIUM 30 [hp_X]/5 mL; IODINE 30 [hp_X]/5 mL; LANTHANUM 30 [hp_X]/5 mL; LITHIUM CARBONATE 30 [hp_X]/5 mL; MANGANESE 30 [hp_X]/5 mL; MERCURIUS SOLUBILIS 30 [hp_X]/5 mL; MOLYBDENUM 30 [hp_X]/5 mL; NEODYMIUM 30 [hp_X]/5 mL; NICKEL 30 [hp_X]/5 mL; NIOBIUM 30 [hp_X]/5 mL; NITROUS OXIDE 30 [hp_X]/5 mL; OXYGEN 30 [hp_X]/5 mL; LEAD 30 [hp_X]/5 mL; PRASEODYMIUM 30 [hp_X]/5 mL; RUBIDIUM 30 [hp_X]/5 mL; SAMARIUM 30 [hp_X]/5 mL; SCANDIUM 30 [hp_X]/5 mL; SELENIUM 30 [hp_X]/5 mL; SILICON DIOXIDE 30 [hp_X]/5 mL; TIN 30 [hp_X]/5 mL; STRONTIUM CARBONATE 30 [hp_X]/5 mL; TANTALUM 30 [hp_X]/5 mL; TERBIUM 30 [hp_X]/5 mL; THULIUM 30 [hp_X]/5 mL; TITANIUM 30 [hp_X]/5 mL; VANADIUM 30 [hp_X]/5 mL; YTTERBIUM 30 [hp_X]/5 mL; ZINC 30 [hp_X]/5 mL; VERATRUM ALBUM ROOT 30 [hp_C]/5 mL; APIS MELLIFERA 30 [hp_C]/5 mL
INACTIVE INGREDIENTS: CITRIC ACID MONOHYDRATE; WATER; ALCOHOL; SODIUM BENZOATE

Active Ingredients

Active Ingredients: Allium sativum 4X-30C, Aurum metallicom 12-30X, Belladonna 30C, Berberis vulgaris 30C, Causticum 30C, Cornium maculatum 30 C, Hepar sulphuris calcareum 30C, Hypericum perforatum 30C, Ipecacuanha 30C, Metal Isode 12-30X (Aluminum, Argentum metallicum, Arsenicum metallicum, Baryta carbonica, Beryllium metallicum, Boron, Bromium, Cadmium metallicum, Carboneum, Cerium, Cesium, Chromium, Cobalt, Cuprum metallicum, Dysprosium, Erbium, Europium, Ferrum metallicum, Fluorine, Gadolinium, Gallium, Germanium metallicum, Holmium, Hydrogen, Indium metallicum, Iodium, Lanthanum, Lithium carbonicum, Manganum metallicum, Mercurius solubillis, Molydbenum, Neodymium, Niccolum metallicum, Niobium, Nitrogenum, Oxygen, Plumburm metallicum, Praseodymium, Rubidium, Samarium, Scandium, Selenium metallicum, Silicea, Stannum metallicum, Strontium carbonicum, Tantalum, Terbium, Thulium, Titanium metallium, Vanadlum, Ytterbium, Zincum metallium), Veratrum album 30C, Apis mellifica 30C.

Inactive Ingredients

Citric acid, Demineralized Water, Ethanol and Sodium benzoate

Directions

Directions: One (1) teaspoon twice daily or as otherwise directed by a healthcare professional. Consult a physician for use in children under 6 years of age.

Indications

Indications: Temporary relief of neurological disorders, vomiting, prostration and metallic aftertaste. Remedy #7 supports detoxification of environmental pollutants.

Keep Out Of Reach Of Children

In case of overdose, get medical help or contact a Poison Control Center right away.

Purpose

Heavy Metal Detox

Warnings

Warnings: If symptoms persist or worsen, seek the advice of a healthcare professional.
Caution: Not recommended for pregnant or lactating women.

Package Label

21st CENTURY HOMEOPATHICS
HOMEOPATHIC REMEDY #7 Heavy Metal Detox
Water Based Formula (0.035 % Ethanol) 4 fl. oz. (120 ml)
Tamper Seal: Sealed for your protection with clear, full body seal. Do not use if seal is missing or broken.
Rev. 10/09 Manufactured for 21st Century Homeopathics Rosenberg,TX 77471 (281) 344-0909 A subsidiary of Biotics Research Corporation